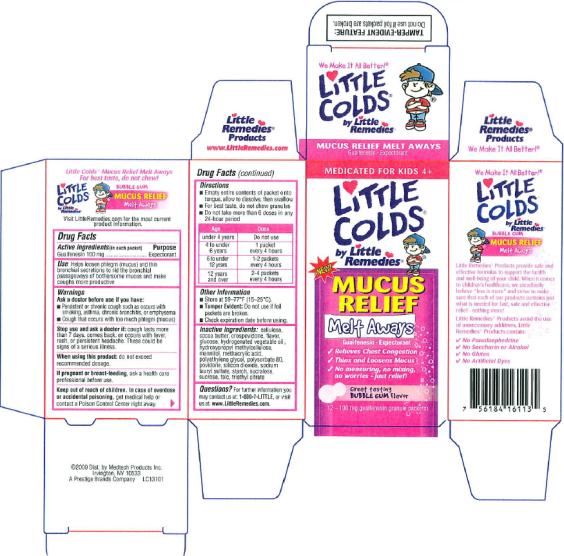 DRUG LABEL: Little Remedies Little Colds Mucus Relief Expectorant Melt Aways
NDC: 63029-101 | Form: GRANULE
Manufacturer: Medtech Products Inc.
Category: otc | Type: HUMAN OTC DRUG LABEL
Date: 20091218

ACTIVE INGREDIENTS: GUAIFENESIN 100 mg/1 1

Little Colds Mucus Relief Melt Aways

Brand: Little Remedies

Product Name: Little Colds Mucus Relief Melt Aways

Size: 12 packets

Country: USA

Artwork Description: IFC

Artwork #: LC13101

Active ingredients

Guaifenesin 100 mg (in each packet)

Purpose

Expectorant

Use

Helps loosen phlegm (mucus) and thin bronchial secretions to rid the bronchial passageways of bothersome mucus and make coughs more productive

Warnings

Ask a doctor before use if you have:

- Persistent or chronic cough such as occurs with smoking, asthma, chronic bronchitis, or emphysema
- Cough that occurs with too much phlegm (mucus)

Stop Use and ask a doctor if:

Cough lasts more than 7 days, comes back, or occurs with fever, rash, or persistent headache. These could be signs of a serious illness.

When using this product:

Do not exceed recommended dosage.

If pregnant or breast-feeding

Ask a health care professional before use.

Keep out of reach of children.

In case of overdose or accidental poisoning, get medical help or contact a Poison Control Center right away.

Directions

- Empty entire contents of packet onto tongue, allow to dissolve, then swallow
- For best taste, do not chew granules
- Do not take more than 6 doses in any 24-hour period

Age | Dose
Under 4 years | Do not use
4 – under 6 years | 1 packet every 4 hours
6 to under 12 years | 1 – 2 packets every 4 hours
12 years and over | 2 – 4 packets every 4 hours

Other Information

- Store at 59–77°F (15–25°C).
- Tamper Evident: Do not use if package has been disturbed or opened.
- Check expiration date before using.

Inactive Ingredients

cellulose, cocoa butter, crospovidone, flavor, glucose, hydrogenated vegetable oil, hydroxypropyl methylcellulose, mannitol, methacrylic acid, polyethylene glycol, polysorbate 80, povidone, silicon dioxide, sodium lauryl sulfate, starch, sucralose, sucrose, talc, triethyl citrate

Questions

For further information you may contact us at: 1-800-7-LITTLE, or visit us at www.LittleRemedies.com.

©2009 Dist. by Medtech Products Inc.

Irvington, NY 10533

A Prestige Brands Company

LC13101

PRINCIPAL DISPLAY PANEL

MEDICATED FOR KIDS 2+

LITTLE

Colds®

By Little

Remedies

NEW!

MUCUS

RELIEF

Melt Aways

Guaifenesin Expectorant

- Relives Chest Congestion
- Thins and Loosens Mucus
- No measuring, no mixing,
  no worries – just relief!

Great tasting

BUBBLE GUM flavor

12 - 100 mg guaifenesin granule packets